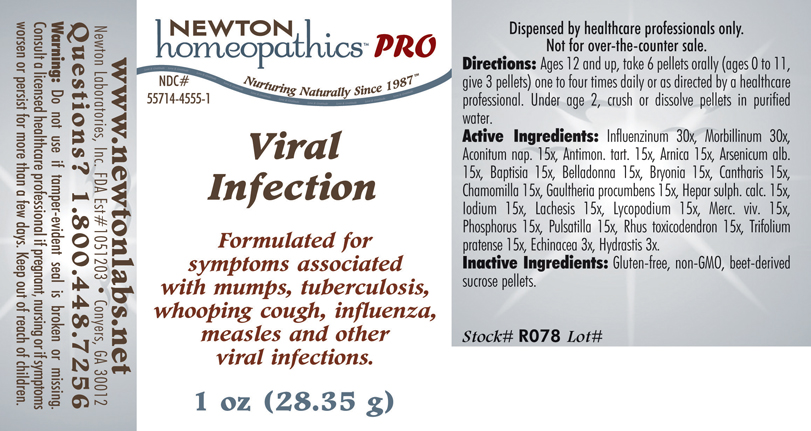 DRUG LABEL: Viral Infection 
NDC: 55714-4555 | Form: PELLET
Manufacturer: Newton Laboratories, Inc.
Category: homeopathic | Type: HUMAN PRESCRIPTION DRUG LABEL
Date: 20110601

ACTIVE INGREDIENTS: Influenza A Virus 30 [hp_X]/1 g; Influenza B Virus 30 [hp_X]/1 g; Measles Virus 30 [hp_X]/1 g; Aconitum Napellus 15 [hp_X]/1 g; Antimony Potassium Tartrate 15 [hp_X]/1 g; Arnica Montana 15 [hp_X]/1 g; Arsenic Trioxide 15 [hp_X]/1 g; Baptisia Tinctoria Root 15 [hp_X]/1 g; Atropa Belladonna 15 [hp_X]/1 g; Bryonia Alba Root 15 [hp_X]/1 g; Lytta Vesicatoria 15 [hp_X]/1 g; Matricaria Recutita 15 [hp_X]/1 g; Gaultheria Procumbens Top 15 [hp_X]/1 g; Calcium Sulfide 15 [hp_X]/1 g; Iodine 15 [hp_X]/1 g; Lachesis Muta Venom 15 [hp_X]/1 g; Lycopodium Clavatum Spore 15 [hp_X]/1 g; Mercury 15 [hp_X]/1 g; Phosphorus 15 [hp_X]/1 g; Pulsatilla Vulgaris 15 [hp_X]/1 g; Toxicodendron Pubescens Leaf 15 [hp_X]/1 g; Trifolium Pratense Flower 15 [hp_X]/1 g; Echinacea, Unspecified 3 [hp_X]/1 g; Goldenseal 3 [hp_X]/1 g
INACTIVE INGREDIENTS: Sucrose

Viral Infection

INDICATIONS & USAGE SECTION

Viral Infection Formulated for symptoms associated with mumps, tuberculosis, whooping cough, influenza, measles and other viral infections.

DOSAGE & ADMINISTRATION SECTION

Directions: Ages 12 and up, take 6 pellets orally (ages 0 to 11, give 3 pellets) one to four times daily or as directed by a healthcare professional. Under age 2, crush or dissolve pellets in purified water.

ACTIVE INGREDIENT SECTION

Influenzinum 30x, Morbillinum 30x, Aconitum nap. 15x, Antimon. tart. 15x, Arnica 15x, Arsenicum alb. 15x, Baptisia 15x, Belladonna 15x, Bryonia 15x, Cantharis 15x, Chamomilla 15x, Gaultheria procumbens 15x, Hepar sulph. calc.15x, Iodium 15x, Lachesis 15x, Lycopodium 15x, Merc. viv. 15x, Phosphorus 15x, Pulsatilla 15x, Rhus toxicodendron 15x, Trifolium pratense 15x, Echinacea 3x, Hydrastis 3x.

PURPOSE SECTION

Formulated for symptoms associated with mumps, tuberculosis, whooping cough, influenza, measles and other viral infections.

INACTIVE INGREDIENT SECTION

Gluten-free, non-GMO, beet-derived sucrose pellets.

QUESTIONS? SECTION

www.newtonlabs.net Newton Laboratories, Inc. FDA Est # 1051203 - Conyers, GA 30012 Questions? 1.800.448.7256

WARNINGS SECTION

Warning: Do not use if tamper - evident seal is broken or missing. Consult a licensed healthcare professional if pregnant, nursing or if symptoms worsen or persist for more than a few days. Keep out of reach of children.

PREGNANCY OR BREAST FEEDING SECTION

Consult a licensed healthcare professional if pregnant, nursing or if symptoms worsen or persist for more than a few days.

KEEP OUT OF REACH OF CHILDREN SECTION

Keep out of reach of children.